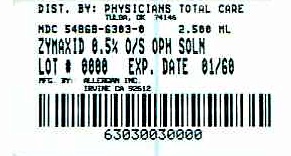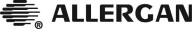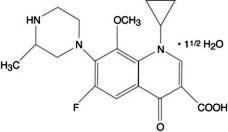 DRUG LABEL: ZYMAXID
NDC: 54868-6303 | Form: SOLUTION/ DROPS
Manufacturer: Physicians Total Care, Inc.
Category: prescription | Type: HUMAN PRESCRIPTION DRUG LABEL
Date: 20120206

ACTIVE INGREDIENTS: gatifloxacin 5 mg/1 mL
INACTIVE INGREDIENTS: edetate disodium; water; sodium chloride; benzalkonium chloride; hydrochloric acid; sodium hydroxide

HIGHLIGHTS OF PRESCRIBING INFORMATION

These highlights do not include all the information needed to use ZYMAXID® safely and effectively. See full prescribing information for ZYMAXID®.
ZYMAXID® (gatifloxacin ophthalmic solution) 0.5%
Initial U.S. Approval: 1999

1 INDICATIONS AND USAGE

ZYMAXID® ophthalmic solution is a topical fluoroquinolone anti-infective indicated for the treatment of bacterial conjunctivitis caused by susceptible strains of the following organisms:

Haemophilus influenzae, Staphylococcus aureus, Staphylococcus epidermidis, Streptococcus mitis group*, Streptococcus oralis*, Streptococcus pneumoniae

*Efficacy for this organism was studied in fewer than 10 infections. (1)

2 DOSAGE AND ADMINISTRATION

Patients 1 year of age or older: Instill one drop every two hours in the affected eye(s) while awake, up to 8 times on Day 1. Instill one drop two to four times daily in the affected eye(s) while awake on Days 2 through 7. (2)

3 DOSAGE FORMS AND STRENGTHS

5 mL size bottle filled with 2.5 mL of gatifloxacin ophthalmic solution, 0.5%. (3)

4 CONTRAINDICATIONS

None

5 WARNINGS AND PRECAUTIONS

- Topical Ophthalmic Use Only (5.1)
- Growth of Resistant Organisms with Prolonged Use (5.2)
- Avoidance of Contact Lenses. Patients should not wear contact lenses if they have signs or symptoms of bacterial conjunctivitis or during the course of therapy with ZYMAXID® (5.3)

6 ADVERSE REACTIONS

Most common adverse reactions occurring in ≥ 1 % of patients included worsening of conjunctivitis, eye irritation, dysgeusia, and eye pain. (6)

To report SUSPECTED ADVERSE REACTIONS, contact Allergan at 1-800-433-8871 or FDA at 1-800-FDA-1088 or www.fda.gov/medwatch.

FULL PRESCRIBING INFORMATION

1 INDICATIONS AND USAGE

ZYMAXID® (gatifloxacin ophthalmic solution) 0.5% solution is indicated for the treatment of bacterial conjunctivitis caused by susceptible strains of the following organisms:

Aerobic Gram-Positive Bacteria:

Staphylococcus aureus
Staphylococcus epidermidis
Streptococcus mitis group*
Streptococcus oralis*
Streptococcus pneumoniae

Aerobic Gram-Negative Bacteria:

Haemophilus influenzae

*Efficacy for this organism was studied in fewer than 10 infections.

2 DOSAGE AND ADMINISTRATION

Patients 1 year of age or older: Instill one drop every two hours in the affected eye(s) while awake, up to 8 times on Day 1. Instill one drop two to four times daily in the affected eye(s) while awake on Days 2 through 7.

3 DOSAGE FORMS AND STRENGTHS

Five (5) mL bottle containing 2.5 mL of a 0.5% sterile topical ophthalmic solution.

4 CONTRAINDICATIONS

None

5 WARNINGS AND PRECAUTIONS

5.1 Topical Ophthalmic Use Only

ZYMAXID® solution should not be introduced directly into the anterior chamber of the eye.

5.2 Growth of Resistant Organisms with Prolonged Use

As with other anti-infectives, prolonged use of ZYMAXID® (gatifloxacin ophthalmic solution) 0.5% may result in overgrowth of nonsusceptible organisms, including fungi. If superinfection occurs, discontinue use and institute alternative therapy. Whenever clinical judgment dictates, the patient should be examined with the aid of magnification, such as slit lamp biomicroscopy and where appropriate, fluoroscein staining.

5.3 Avoidance of Contact Lens Wear

Patients should be advised not to wear contact lenses if they have signs and symptoms of bacterial conjunctivitis or during the course of therapy with ZYMAXID® (see PATIENT COUNSELING INFORMATION, 17.2).

6 ADVERSE REACTIONS

6.1 Clinical Studies Experience

Because clinical studies are conducted under widely varying conditions, adverse reaction rates observed in the clinical studies of a drug cannot be directly compared to rates in the clinical studies of another drug and may not reflect the rates observed in practice.

In clinical studies with ZYMAXID®, the most frequently reported adverse reactions occurring in ≥ 1% of patients in the gatifloxacin study population (N=717) were: worsening of the conjunctivitis, eye irritation, dysgeusia, and eye pain.

Additional adverse events reported with other formulations of gatifloxacin ophthalmic solution include chemosis, conjunctival hemorrhage, dry eye, eye discharge, eyelid edema, headache, increased lacrimation, keratitis, papillary conjunctivitis, and reduced visual acuity.

7 DRUG INTERACTIONS

Specific drug interaction studies have not been conducted with ZYMAXID® ophthalmic solution.

8 USE IN SPECIFIC POPULATIONS

8.1 Pregnancy

Pregnancy Category C

Teratogenic Effects: There were no teratogenic effects observed in rats or rabbits following oral gatifloxacin doses up to 50 mg/kg/day (approximately 1000-fold higher than the maximum recommended ophthalmic dose). However, skeletal/craniofacial malformations or delayed ossification, atrial enlargement, and reduced fetal weight were observed in fetuses from rats given ≥150 mg/kg/day (approximately 3000-fold higher than the maximum recommended ophthalmic dose). In a perinatal/postnatal study, increased late post-implantation loss and neonatal/perinatal mortalities were observed at 200 mg/kg/day (approximately 4000-fold higher than the maximum recommended ophthalmic dose).

Because there are no adequate and well-controlled studies in pregnant women, ZYMAXID® solution should be used during pregnancy only if the potential benefit justifies the potential risk to the fetus.

8.3 Nursing Mothers

Gatifloxacin is excreted in the breast milk of rats. It is not known whether this drug is excreted in human milk. Because many drugs are excreted in human milk, caution should be exercised when ZYMAXID® is administered to a nursing woman.

8.4 Pediatric Use

The safety and effectiveness of ZYMAXID® in infants below one year of age have not been established. ZYMAXID® has been demonstrated in clinical trials to be safe and effective for the treatment of bacterial conjunctivitis in pediatric patients one year or older (see CLINICAL STUDIES, 14).

8.5 Geriatric Use

No overall differences in safety or effectiveness have been observed between elderly and younger patients.

11 DESCRIPTION

ZYMAXID® sterile ophthalmic solution is an 8-methoxyfluoroquinolone anti-infective for the treatment of bacterial conjunctivitis. Its chemical name is (±)-1-Cyclopropyl-6-fluoro-1,4-dihydro-8-methoxy-7-(3-methyl-1-piperazinyl)-4-oxo-3-quinolinecarboxylic acid, sesquihydrate. Its molecular formula is C19H22FN3O4 · 1½H2O, and its molecular weight is 402.42. Its chemical structure is:

ZYMAXID® is a clear, pale yellow, sterile, preserved aqueous solution with an osmolality of 260-330 mOsm/kg and a pH of 5.1-5.7.

ZYMAXID® contains Active: gatifloxacin 0.5% (5 mg/mL); Inactives: benzalkonium chloride 0.005%; edetate disodium; purified water; and sodium chloride. May contain hydrochloric acid and/or sodium hydroxide to adjust pH.

12 CLINICAL PHARMACOLOGY

12.1 Mechanism of Action

Gatifloxacin is a fluoroquinolone antibacterial (see CLINICAL PHARMACOLOGY, 12.4).

12.3 Pharmacokinetics

Gatifloxacin ophthalmic solution 0.3% or 0.5% was administered to one eye of 6 healthy male subjects each in an escalated dosing regimen starting with a single 2 drop dose, then 2 drops 4 times daily for 7 days, and finally 2 drops 8 times daily for 3 days. At all time points, serum gatifloxacin levels were below the lower limit of quantification (5 ng/mL) in all subjects.

12.4 Microbiology

Gatifloxacin is an 8-methoxyfluoroquinolone with a 3-methylpiperazinyl substituent at C7. The antibacterial action of gatifloxacin results from inhibition of DNA gyrase and topoisomerase IV. DNA gyrase is an essential enzyme that is involved in the replication, transcription, and repair of bacterial DNA. Topoisomerase IV is an enzyme known to play a key role in the partitioning of the chromosomal DNA during bacterial cell division. The mechanism of action of fluoroquinolones including gatifloxacin is different from that of aminoglycoside, macrolide, and tetracycline antibiotics. Therefore, gatifloxacin may be active against pathogens that are resistant to these antibiotics and these antibiotics may be active against pathogens that are resistant to gatifloxacin. There is no cross-resistance between gatifloxacin and the aforementioned classes of antibiotics. Cross resistance has been observed between systemic gatifloxacin and some other fluoroquinolones.

Resistance to gatifloxacin in vitro develops via multiple-step mutations. Resistance to gatifloxacin in vitro occurs at a general frequency of 1 x 10^-7 to 10^-10.

Gatifloxacin has been shown to be active against most isolates of the following organisms both microbiologically and clinically, in conjunctival infections as described in the INDICATIONS AND USAGE, Section 1.

Aerobic Gram-Positive Bacteria:

Staphylococcus aureus
Staphylococcus epidermidis
Streptococcus mitis group*
Streptococcus oralis*
Streptococcus pneumoniae

Aerobic Gram-Negative Bacteria:

Haemophilus influenzae

*Efficacy for this organism was studied in fewer than 10 infections.

13 NONCLINICAL TOXICOLOGY

13.1 Carcinogenesis, Mutagenesis, Impairment of Fertility

There was no increase in neoplasms among B6C3F1 mice given gatifloxacin in the diet for 18 months at doses averaging 81 mg/kg/day in males and 90 mg/kg/day in females. These doses are approximately 1600-fold and 1800-fold higher, respectively, than the maximum recommended ophthalmic dose of 0.05 mg/kg/day in a 50 kg human.

There was no increase in neoplasms among Fischer 344 rats given gatifloxacin in the diet for 2 years at doses averaging 47 mg/kg/day in males and 139 mg/kg/day in females (900- and 2800-fold higher, respectively, than the maximum recommended ophthalmic dose). A statistically significant increase in the incidence of large granular lymphocyte (LGL) leukemia was seen in males treated with a high dose of approximately 2000-fold higher than the maximum recommended ophthalmic dose. Fischer 344 rats have a high spontaneous background rate of LGL leukemia and the incidence in high-dose males only slightly exceeded the historical control range established for this strain.

In genetic toxicity tests, gatifloxacin was positive in 1 of 5 strains used in bacterial reverse mutation assays: Salmonella strain TA102. Gatifloxacin was positive in in vitro mammalian cell mutation and chromosome aberration assays. Gatifloxacin was positive in in vitro unscheduled DNA synthesis in rat hepatocytes but not human leukocytes. Gatifloxacin was negative in in vivo micronucleus tests in mice, cytogenetics test in rats, and DNA repair test in rats. The findings may be due to the inhibitory effects of high concentrations on eukaryotic type II DNA topoisomerase.

There were no adverse effects on fertility or reproduction in rats given gatifloxacin orally at doses up to 200 mg/kg/day (approximately 4000-fold higher than the maximum recommended ophthalmic dose for ZYMAXID®).

14 CLINICAL STUDIES

In two randomized, double-masked, multicenter clinical trials, where patients 1-89 years of age were dosed for 5 days, ZYMAXID® solution was clinically superior to its vehicle on day 6 in patients with conjunctivitis and positive conjunctival cultures. Clinical outcomes for the trials demonstrated clinical success (resolution of conjunctival hyperaemia and conjunctival discharge) of 58% (193/333) for the gatifloxacin-treated groups versus 45% (148/325) for the vehicle-treated groups. Microbiological outcomes for the same clinical trials demonstrated a statistically superior eradication rate for causative pathogens of 90% (301/333) for gatifloxacin versus 70% (228/325) for vehicle. Please note that microbiological eradication does not always correlate with clinical outcome in anti-infective trials.

16 HOW SUPPLIED/STORAGE AND HANDLING

ZYMAXID® (gatifloxacin ophthalmic solution) 0.5% is supplied sterile in a white, low density polyethylene (LDPE) bottle with a controlled dropper tip, and a tan, high impact polystyrene (HIPS) cap in the following size:

2.5 mL in 5 mL bottle: NDC 54868-6303-0

STORAGE AND HANDLING

Storage: Store at 15°-25°C (59°-77°F). Protect from freezing.

17 PATIENT COUNSELING INFORMATION

17.1 Avoiding Contamination of the Product

Patients should be instructed to avoid contaminating the applicator tip with material from the eye, fingers, or other source.

17.2 Avoidance of Contact Lens Wear

Patients should be advised not to wear contact lenses if they have signs and symptoms of bacterial conjunctivitis.

© 2012 Allergan, Inc.
Irvine, CA 92612, U.S.A.
® marks owned by Allergan, Inc.
Licensed from Kyorin Pharmaceuticals Co., Ltd.
U.S. Patents 5,880,283 and 6,333,045

Made in the U.S.A.

72366US11C

Additional barcode labeling by:
Physicians Total Care, Inc.
Tulsa, Oklahoma 74146

PRINCIPAL DISPLAY PANEL

Package Label – 2.5 mL Carton Label

NDC 54868-6303-0

Zymaxid®

(gatifloxacin ophthalmic solution) 0.5%

2.5 mL

Rx only sterile